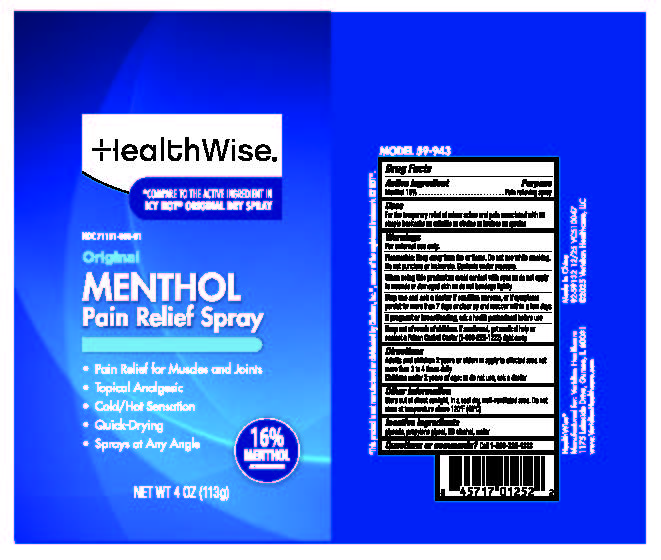 DRUG LABEL: HealthWise Original Menthol
NDC: 71101-080 | Form: SPRAY
Manufacturer: Veridian Healthcare
Category: otc | Type: HUMAN OTC DRUG LABEL
Date: 20251217

ACTIVE INGREDIENTS: MENTHOL 16 g/100 mL
INACTIVE INGREDIENTS: ALCOHOL 95%; PROPYLENE GLYCOL; GLYCERIN; WATER

HealthWise 16% Menthol Pain Relief Spray

Drug Facts

Menthol 16%

PURPOSE

External analgesic

Uses

for temporary relief of minor pain and associated with:

- arthritis
- simple backache
- muscle strains
- sprains
- bruises

Warnings

For external use only

Flammable Do not use while smoking or near heat of flame.

Stop use and ask a doctor

- condition worsens
- rash or irritation develops and lasts for more than 7 days or clear up and occur again withing a few days

When using this product

- keep out of eyes. In case of contact with eyes, flush thoroughly with water
- avoid contact with broken skin
- do not bandage tightly
- do not use with heating pad
- contents under pressure. Do not punture or incinerate. Do not store at temperature above 120 F

Stop use and ask a doctor if

- condition worsens
- rash or irritation develops and last for more than 7 days or clear up and occur again within a few days

Keep out of reach of children.

If swallowed, get medical help or contact a Poison Control Center (1-800-222-1222) right away.

Directions

- adults and children 2 years and older:apply to affected area not more than 3 to 4 times daily.
- children under 2 years of age:do not use, ask a doctor

Other information

- Store out of direct sunlight, in a cool dry well-ventilated area

Inactive ingredients

glycerine, propylene glycol, SD alcohol, water